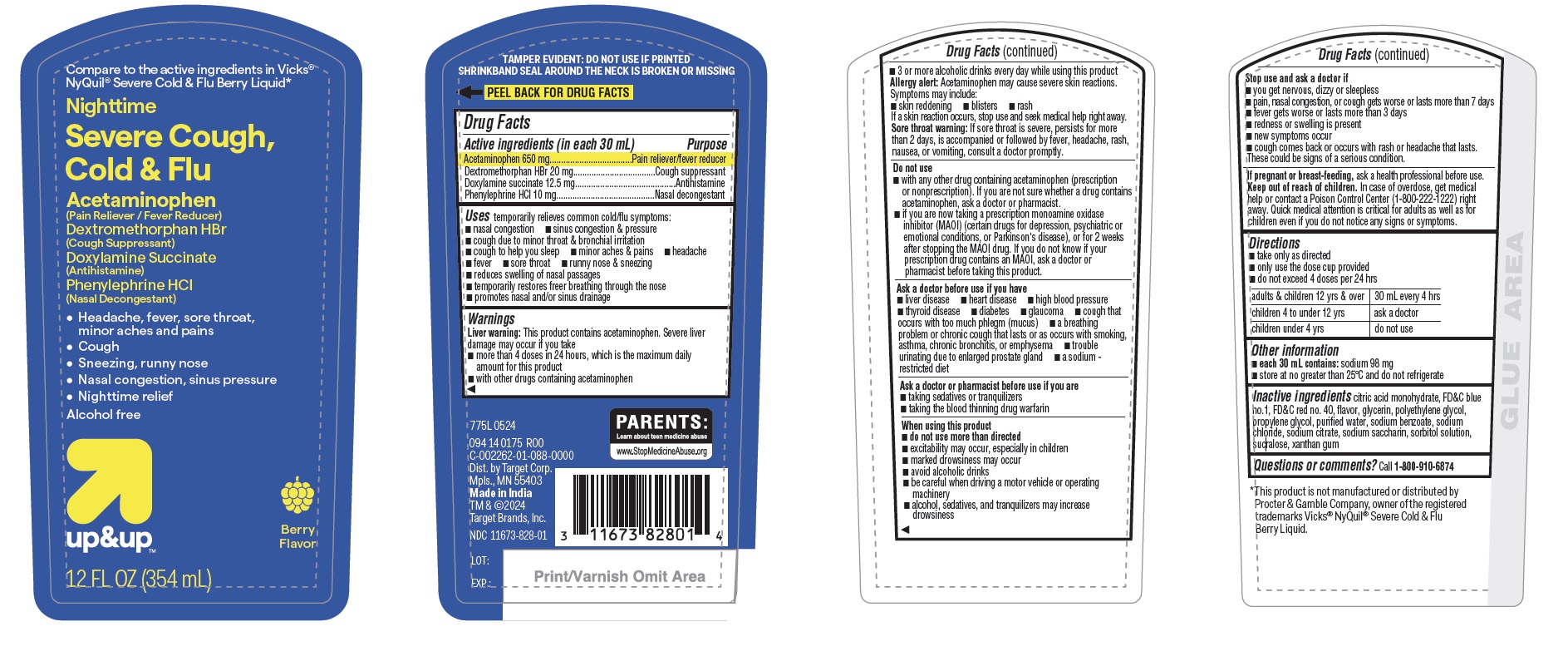 DRUG LABEL: Nighttime severe cold and flu
NDC: 11673-828 | Form: LIQUID
Manufacturer: TARGET CORPORATION
Category: otc | Type: HUMAN OTC DRUG LABEL
Date: 20240711

ACTIVE INGREDIENTS: DEXTROMETHORPHAN HYDROBROMIDE 20 mg/30 mL; ACETAMINOPHEN 650 mg/30 mL; DOXYLAMINE SUCCINATE 12.5 mg/30 mL; PHENYLEPHRINE HYDROCHLORIDE 10 mg/30 mL
INACTIVE INGREDIENTS: PROPYLENE GLYCOL; FD&C BLUE NO. 1; SODIUM BENZOATE; SODIUM CHLORIDE; SODIUM CITRATE; XANTHAN GUM; SORBITOL SOLUTION; WATER; SACCHARIN SODIUM; FD&C RED NO. 40; SUCRALOSE; GLYCERIN; CITRIC ACID MONOHYDRATE; POLYETHYLENE GLYCOL, UNSPECIFIED

775L - Target - Nighttime Severe Liquid Berry

Active ingredients (in each 30 mL)

Acetaminophen 650 mg
Dextromethorphan HBr 20 mg
Doxylamine succinate 12.5 mg
Phenylephrine HCl 10 mg

Purpose

Pain reliever/fever reducer
Cough suppressant
Antihistamine
Nasal decongestant

Uses

temporarily relieves common cold/flu symptoms:

- nasal congestion
- sinus congestion & pressure
- cough due to minor throat & bronchial irritation
- cough to help you sleep
- minor aches & pains
- headache
- fever
- sore throat
- runny nose & sneezing
- reduces swelling of nasal passages
- temporarily restores freer breathing through the nose
- promotes nasal and/or sinus drainage

WARNINGS

Liver warning: This product contains acetaminophen. Severe liver damage may occur if you take
• more than 4 doses in 24 hours, which is the maximum daily amount for this product
• with other drugs containing acetaminophen
• 3 or more alcoholic drinks every day while using this product

Allergy alert: Acetaminophen may cause severe skin reactions. Symptoms may include:
• skin reddening
• blisters
• rash
If a skin reaction occurs, stop use and seek medical help right away.

Sore throat warning: If sore throat is severe, persists for more than 2 days, is accompanied or followed by fever, headache, rash, nausea, or vomiting, consult a doctor promptly.

Do not use
• with any other drug containing acetaminophen (prescription or nonprescription). If you are not sure whether a drug contains acetaminophen, ask a doctor or pharmacist.
• if you are now taking a prescription monoamine oxidase inhibitor (MAOI) (certain drugs for depression, psychiatric or emotional conditions, or Parkinson's disease), or for 2 weeks after stopping the MAOI drug. If you do not know if your prescription drug contains an MAOI, ask a doctor or pharmacist before taking this product.

Ask a doctor before use if you have
• liver disease
• heart disease
• high blood pressure
• thyroid disease
• diabetes
• glaucoma
• cough that occurs with too much phlegm (mucus)
• a breathing problem or chronic cough that lasts or as occurs with smoking, asthma, chronic bronchitis, or emphysema
• trouble urinating due to enlarged prostate gland
• a sodium-restricted diet

Ask a doctor or pharmacist before use if you are
• taking sedatives or tranquilizers
• taking the blood thinning drug warfarin.

When using this product
• do not use more than directed
• excitability may occur, especially in children
• marked drowsiness may occur
• avoid alcoholic drinks
• be careful when driving a motor vehicle or operating machinery
• alcohol, sedatives, and tranquilizers may increase drowsiness

Stop use and ask a doctor if
• you get nervous, dizzy or sleepless
• pain, nasal congestion, or cough gets worse or lasts more than 7 days
• fever gets worse or lasts more than 3 days
• redness or swelling is present
• new symptoms occur
• cough comes back or occurs with rash or headache that lasts.
These could be signs of a serious condition.

PREGNANCY OR BREAST FEEDING

If pregnant or breastfeeding, ask a health professional before use.

Keep out of reach of children. In case of overdose, get medical help or contact a Poison Control Center (1-800-222-1222) right away. Quick medical attention is critical for adults as well as for children even if you do not notice any signs or symptoms.

Directions
• take only as directed
• only use the dose cup provided
• do not exceed 4 doses per 24 hrs

adults & children 12 yrs & over | 30 mL every 4 hrs
children 4 to under 12 yrs | ask a doctor
children under 4 yrs | do not use

Other information
• each 30 mL contains: sodium 98 mg
• store at no greater than 25℃ and do not refrigerate

INACTIVE INGREDIENT

Inactive ingredients citric acid monohydrate, FD&C blue no.1, FD&C red no. 40, flavor, glycerin, polyethylene glycol, propylene glycol, purified water, sodium benzoate, sodium chloride, sodium citrate, sodium saccharin, sorbitol solution, sucralose, xanthan gum

Questions or comments? Call 1-800-910-6874